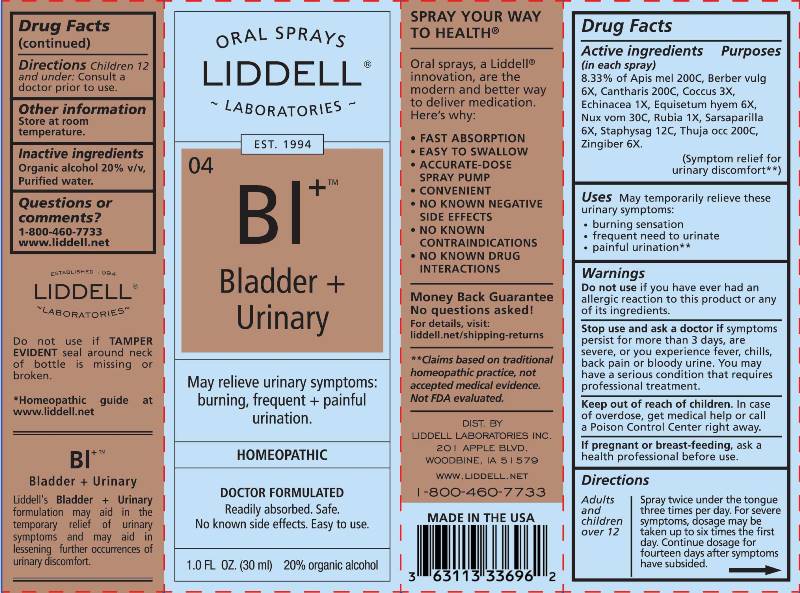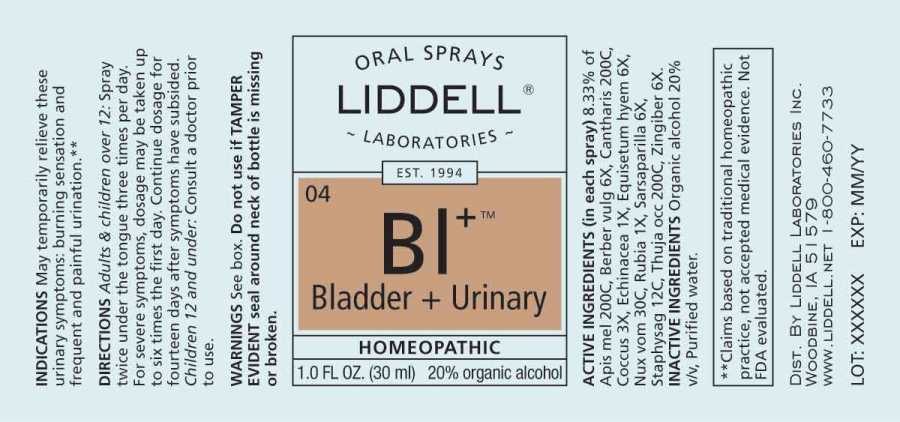 DRUG LABEL: Bladder Urinary
NDC: 50845-0244 | Form: LIQUID
Manufacturer: Liddell Laboratories, Inc.
Category: homeopathic | Type: HUMAN OTC DRUG LABEL
Date: 20241104

ACTIVE INGREDIENTS: APIS MELLIFERA 200 [hp_C]/1 mL; BERBERIS VULGARIS ROOT BARK 6 [hp_X]/1 mL; LYTTA VESICATORIA 200 [hp_C]/1 mL; PROTORTONIA CACTI 3 [hp_X]/1 mL; ECHINACEA ANGUSTIFOLIA WHOLE 1 [hp_X]/1 mL; EQUISETUM HYEMALE WHOLE 6 [hp_X]/1 mL; STRYCHNOS NUX-VOMICA SEED 30 [hp_C]/1 mL; RUBIA TINCTORUM ROOT 1 [hp_X]/1 mL; SMILAX ORNATA ROOT 6 [hp_X]/1 mL; DELPHINIUM STAPHISAGRIA SEED 12 [hp_C]/1 mL; THUJA OCCIDENTALIS LEAF 200 [hp_C]/1 mL; GINGER 6 [hp_X]/1 mL
INACTIVE INGREDIENTS: WATER; ALCOHOL

DRUG FACTS:

ACTIVE INGREDIENTS:

(in each drop): 8.33% of Apis Mellifica 200C, Berberis Vulgaris 6X, Cantharis 200C, Coccus Cacti 3X, Echinacea (Angustifolia) 1X, Equisetum Hyemale 6X, Nux Vomica 30C, Rubia Tinctorum 1X, Sarsaparilla (Smilax Regelii) 6X, Staphysagria 12C, Thuja Occidentalis 200C, Zingiber Officinale 6X.

USES:

May temporarily relieve these urinary symptoms:

- burning sensation
- frequent need to urinate
- painful urination**

**Claims based on traditional homeopathic practice, not accepted medical evidence. Not FDA evaluated.

WARNINGS:

Do not use if you have ever has an allergic reaction to this product or any of its ingredients.

Stop use and ask a doctor if symptoms persist for more than 3 days, are severe, or you experience fever, chills, back pain or bloody urine.

You may have a serious condition that requires professional treatment.

Keep out of reach of children. In case of overdose, get medical help or call a Poison Control Center right away.

If pregnant or breast-feeding, ask a health professional before use.

Do not use if TAMPER EVIDENT seal around neck of bottle is missing or broken.

Keep out of reach of children. In case of overdose, get medical help or call a Poison Control Center right away.

DIRECTIONS:

Adults and children over 12: Spray twice under the tongue three times per day.

For severe symptoms, dosage may be taken up to six times the first day. Continue dosage for fourteen days after symptoms have subsided.

Children 12 and under: Consult a doctor prior to use.

INDICATIONS:

May temporarily relieve these urinary symptoms:

• burning sensation
• frequent need to urinate
• painful urination**

**Claims based on traditional homeopathic practice, not accepted medical evidence. Not FDA evaluated.

INACTIVE INGREDIENTS:

Organic alcohol 20% v/v, Purified Water.

QUESTIONS:

DIST. BY

LIDDELL LABORATORIES INC.

201 APPLE BLVD.

WOODBINE, IA 51579

WWW.LIDDELL.NET

1-800-460-7733

PACKAGE LABEL DISPLAY:

ORAL SPRAYS

LIDDELL

LABORATORIES

EST 1994

^04 BI^+

Bladder +

Urinary

May relieve urinary symptoms:

burning, frequent + painful

urination.

HOMEOPATHIC

DOCTOR FORMULATED

Readily absorbed. Safe.

No known side effects. Easy to use.

1.0 FL OZ. (30ml)